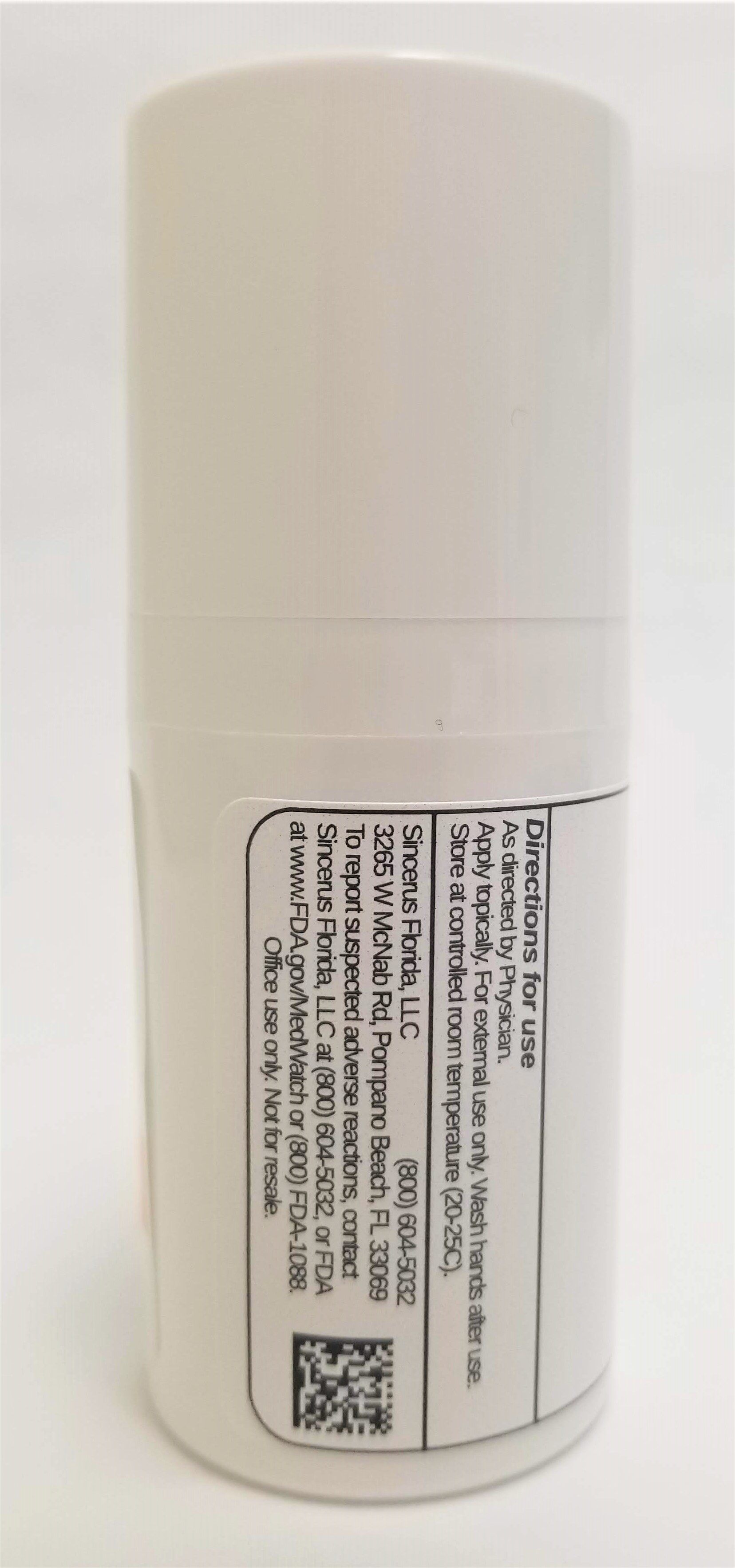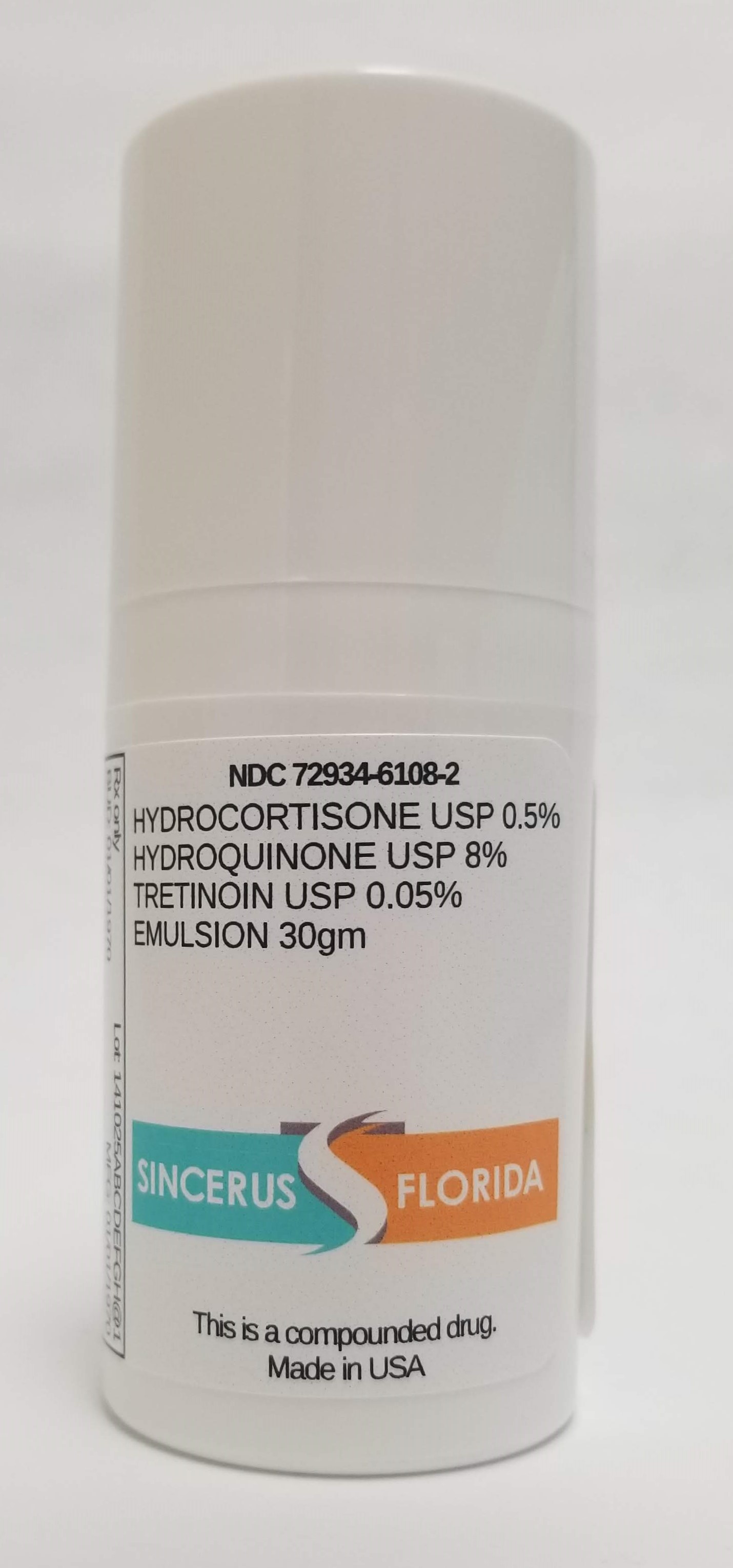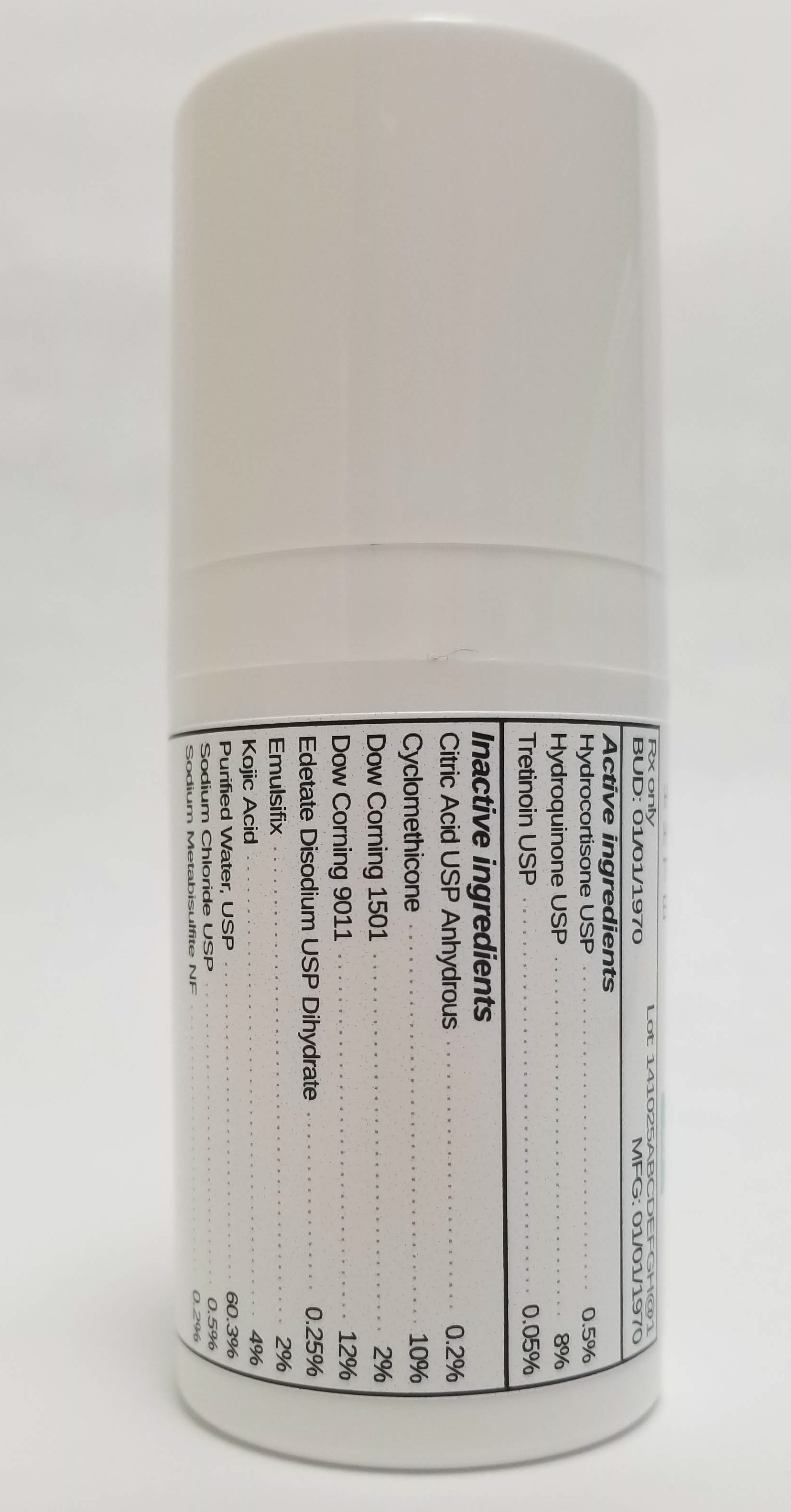 DRUG LABEL: HYDROCORTISONE 0.5% / HYDROQUINONE 8% / TRETINOIN 0.05%
NDC: 72934-6108 | Form: EMULSION
Manufacturer: Sincerus Florida, LLC
Category: prescription | Type: HUMAN PRESCRIPTION DRUG LABEL
Date: 20190517

ACTIVE INGREDIENTS: TRETINOIN 0.05 g/100 g; HYDROCORTISONE 0.5 g/100 g; HYDROQUINONE 8 g/100 g

HYDROCORTISONE 0.5% / HYDROQUINONE 8% / TRETINOIN 0.05%